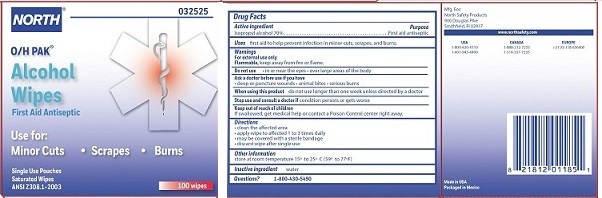 DRUG LABEL: North Alcohol Wipe
NDC: 0498-0140 | Form: SWAB
Manufacturer: North Safety Products
Category: otc | Type: HUMAN OTC DRUG LABEL
Date: 20180702

ACTIVE INGREDIENTS: ISOPROPYL ALCOHOL 0.7 mL/1 mL
INACTIVE INGREDIENTS: WATER

Alcohol Wipes

Drug Facts

Active ingredient

Isopropyl alcohol 70%

Purpose

First aid antiseptic

Uses

first aid to help prevent infection in minor cuts, scrapes, and burns

Warnings

For external use only

Flammable, keep away from fire or flame.

Do not use

- in the eyes
- over large areas of the body

Ask a doctor before use if you have

- deep or puncture wounds
- animal bites
- serious burns

When using this product do not use longer than one week unless directed by a doctor

Stop use and consult a doctor if condition persists or gets worse

Keep out of reach of children

If swallowed, get medical help or contact a Poison Control Center right away.

Directions

- clean the affected area
- apply wipe to affected area 1 to 3 times daily
- may be covered with a sterile bandage
- discard wipe after single use

Other information

store at room temperature 15o to 25o C (59o to 77oF)

Inactive ingredient water

Questions? 1-800-430-5490

Mfg For:

North Safety Products

900 Douglas Pike

Smithfield, RI 02917

www.northsafety.com

USA

1-800-430-4110

1-401-943-4400

Made in USA

Packaged in Mexico

PACKAGE LABEL

NORTH

O/H PAK

Alcohol Wipes

First Aid Antiseptic

Use for:

Minor Cuts, Scrapes, Burns

Single Use Packets

Saturated Wipes

100 Wipes